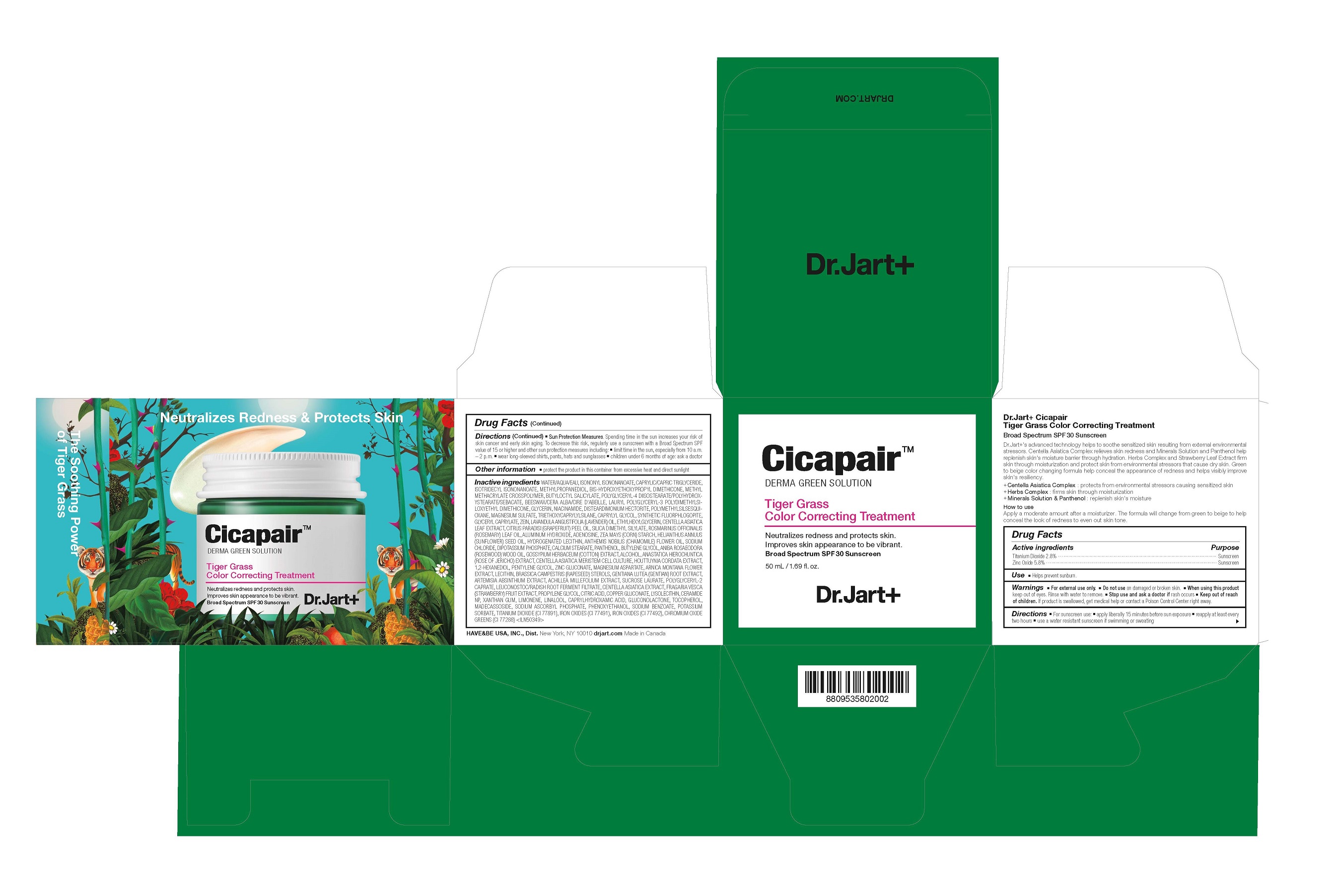 DRUG LABEL: DR.JART CICAPAIR TIGER GRASS COLOR CORRECTING TREATMENT
NDC: 49404-300 | Form: CREAM
Manufacturer: Have & Be Co., Ltd.
Category: otc | Type: HUMAN OTC DRUG LABEL
Date: 20250206

ACTIVE INGREDIENTS: TITANIUM DIOXIDE 28 mg/1 mL; ZINC OXIDE 58 mg/1 mL
INACTIVE INGREDIENTS: PROPYLENE GLYCOL; ZINC GLUCONATE; ALCOHOL; RAPESEED STEROL; ACHILLEA MILLEFOLIUM WHOLE; GENTIANA LUTEA ROOT; CITRIC ACID MONOHYDRATE; LINALOOL, (+/-)-; SUNFLOWER OIL; POLYMETHYLSILSESQUIOXANE (4.5 MICRONS); FERRIC OXIDE RED; TRIETHOXYCAPRYLYLSILANE; MADECASSOSIDE; SODIUM CHLORIDE; HOUTTUYNIA CORDATA FLOWERING TOP; PENTYLENE GLYCOL; MAGNESIUM ASPARTATE; POLYGLYCERYL-2 CAPRATE; CENTELLA ASIATICA WHOLE; PHENOXYETHANOL; COPPER GLUCONATE; GRAPEFRUIT OIL; ISONONYL ISONONANOATE; CAPRYLYL GLYCOL; TOCOPHEROL; WORMWOOD; SUCROSE LAURATE; GLUCONOLACTONE; XANTHAN GUM; SODIUM ASCORBYL PHOSPHATE; LIMONENE, (+)-; ISOTRIDECYL ISONONANOATE; METHYL METHACRYLATE/GLYCOL DIMETHACRYLATE CROSSPOLYMER; GLYCERIN; NIACINAMIDE; GLYCERYL MONOCAPRYLATE; LAVENDER OIL; CENTELLA ASIATICA LEAF; ROSEMARY OIL; ADENOSINE; STARCH, CORN; MEDIUM-CHAIN TRIGLYCERIDES; CHROMIC OXIDE; FERRIC OXIDE YELLOW; ALUMINUM HYDROXIDE; HYDROGENATED SOYBEAN LECITHIN; CHAMAEMELUM NOBILE FLOWER OIL; PANTHENOL; BUTYLENE GLYCOL; CERAMIDE NP; BIS-HYDROXYETHOXYPROPYL DIMETHICONE (37 CST); BUTYLOCTYL SALICYLATE; YELLOW WAX; 1,2-HEXANEDIOL; LEUCONOSTOC/RADISH ROOT FERMENT FILTRATE; LYSOPHOSPHATIDYLCHOLINE, SOYBEAN; SODIUM BENZOATE; POTASSIUM SORBATE; MAGNESIUM SULFATE, UNSPECIFIED; METHYLPROPANEDIOL; DISTEARDIMONIUM HECTORITE; ZEIN; ETHYLHEXYLGLYCERIN; SILICA DIMETHYL SILYLATE; CAPRYLHYDROXAMIC ACID; CALCIUM STEARATE; ROSEWOOD OIL; LEVANT COTTON SEED; ANASTATICA HIEROCHUNTICA WHOLE; ARNICA MONTANA FLOWER; FRAGARIA VESCA FRUIT

DR.JART CICAPAIR TIGER GRASS COLOR CORRECTING TREATMENT

Active ingredients

Titanium Dioxide 2.8%

Zinc Oxide 5.8%

Purpose

Sunscreen

Use

Helps prevent sunburn.

Warnings

For external use only.

Do not use

on damaged or broken skin.

When using this product

keep out of eyes. Rinse with water to remove.

Stop use and ask a doctor if

rash occurs

Keep out of reach of children.

If product is swallowed, get medical help or contact a Poison Control Center right away.

Directions

■ For sunscreen use: ■ apply liberally 15 minutes before sun exposure ■ reapply at least every two hours ■ use a water resistant sunscreen if swimming or sweating ■ Sun Protection Measures. Spending time in the sun increases your risk of skin cancer and early skin aging. To decrease this risk, regularly use a sunscreen with a Broad Spectrum SPF value of 15 or higher and other sun protection measures including: ■ limit time in the sun, especially from 10 a.m. – 2 p.m. ■ wear long-sleeved shirts, pants, hats and sunglasses ■ children under 6 months of age: ask a doctor

Inactive ingredients

Inactive ingredients WATER/AQUA/EAU, ISONONYL ISONONANOATE, CAPRYLIC/CAPRIC TRIGLYCERIDE, ISOTRIDECYL ISONONANOATE, METHYLPROPANEDIOL, BIS-HYDROXYETHOXYPROPYL DIMETHICONE, METHYL METHACRYLATE CROSSPOLYMER, BUTYLOCTYL SALICYLATE, POLYGLYCERYL-4 DIISOSTEARATE/POLYHYDROX-YSTEARATE/SEBACATE, BEESWAX/CERA ALBA/CIRE D'ABEILLE, LAURYL POLYGLYCERYL-3 POLYDIMETHYLSI-LOXYETHYL DIMETHICONE, GLYCERIN, NIACINAMIDE, DISTEARDIMONIUM HECTORITE, POLYMETHYLSILSESQUI-OXANE, MAGNESIUM SULFATE, TRIETHOXYCAPRYLYLSILANE, CAPRYLYL GLYCOL, SYNTHETIC FLUORPHLOGOPITE, GLYCERYL CAPRYLATE, ZEIN, LAVANDULA ANGUSTIFOLIA (LAVENDER) OIL, ETHYLHEXYLGLYCERIN, CENTELLA ASIATICA LEAF EXTRACT, CITRUS PARADISI (GRAPEFRUIT) PEEL OIL, SILICA DIMETHYL SILYLATE, ROSMARINUS OFFICINALIS (ROSEMARY) LEAF OIL, ALUMINUM HYDROXIDE, ADENOSINE, ZEA MAYS (CORN) STARCH, HELIANTHUS ANNUUS (SUNFLOWER) SEED OIL, HYDROGENATED LECITHIN, ANTHEMIS NOBILIS (CHAMOMILE) FLOWER OIL, SODIUM CHLORIDE, DIPOTASSIUM PHOSPHATE, CALCIUM STEARATE, PANTHENOL, BUTYLENE GLYCOL, ANIBA ROSAEODORA (ROSEWOOD) WOOD OIL, GOSSYPIUM HERBACEUM (COTTON) EXTRACT, ALCOHOL, ANASTATICA HIEROCHUNTICA (ROSE OF JERICHO) EXTRACT, CENTELLA ASIATICA MERISTEM CELL CULTURE, HOUTTUYNIA CORDATA EXTRACT, 1,2-HEXANEDIOL, PENTYLENE GLYCOL, ZINC GLUCONATE, MAGNESIUM ASPARTATE, ARNICA MONTANA FLOWER EXTRACT, LECITHIN, BRASSICA CAMPESTRIS (RAPESEED) STEROLS, GENTIANA LUTEA (GENTIAN) ROOT EXTRACT, ARTEMISIA ABSINTHIUM EXTRACT, ACHILLEA MILLEFOLIUM EXTRACT, SUCROSE LAURATE, POLYGLYCERYL-2 CAPRATE, LEUCONOSTOC/RADISH ROOT FERMENT FILTRATE, CENTELLA ASIATICA EXTRACT, FRAGARIA VESCA (STRAWBERRY) FRUIT EXTRACT, PROPYLENE GLYCOL, CITRIC ACID, COPPER GLUCONATE, LYSOLECITHIN, CERAMIDE NP, XANTHAN GUM, LIMONENE, LINALOOL, CAPRYLHYDROXAMIC ACID, GLUCONOLACTONE, TOCOPHEROL, MADECASSOSIDE, SODIUM ASCORBYL PHOSPHATE, PHENOXYETHANOL, SODIUM BENZOATE, POTASSIUM SORBATE, TITANIUM DIOXIDE (CI 77891), IRON OXIDES (CI 77491), IRON OXIDES (CI 77492), CHROMIUM OXIDE GREENS (CI 77288) <ILN50349>

Other information

protect the product in this container from excessive heat and direct sunlight

PACKAGE LABEL

Cicapair

DERMA GREEN SOLUTION

Tiger Grass

Color Correcting Treatment

Neutralizes redness and protects skin.

Improves skin appearance to be vibrant.

Broad Spectrum SPF 30 Sunscreen
50 mL / 1.69 ﬂ. oz.

Dr.Jart+